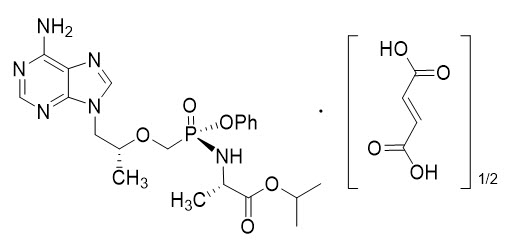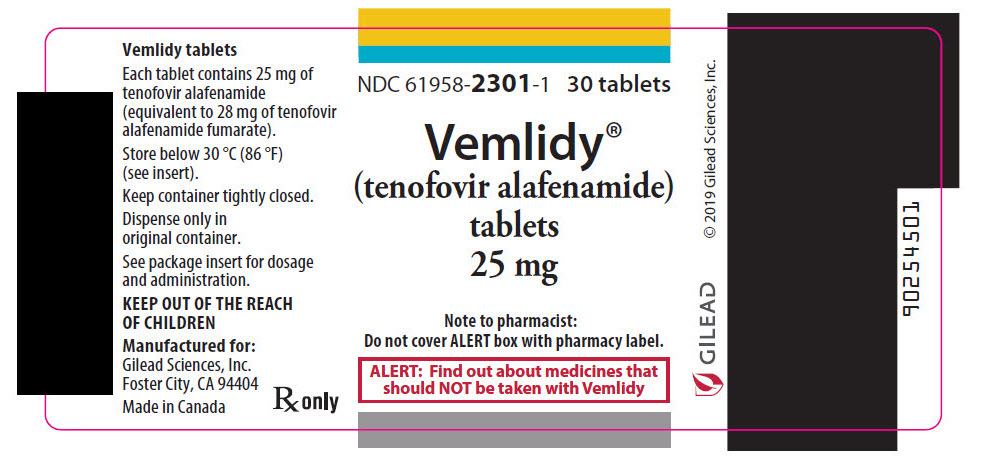 DRUG LABEL: VEMLIDY
NDC: 61958-2301 | Form: TABLET
Manufacturer: Gilead Sciences, Inc.
Category: prescription | Type: HUMAN PRESCRIPTION DRUG LABEL
Date: 20250714

ACTIVE INGREDIENTS: TENOFOVIR ALAFENAMIDE FUMARATE 25 mg/1 1
INACTIVE INGREDIENTS: LACTOSE MONOHYDRATE; MICROCRYSTALLINE CELLULOSE; CROSCARMELLOSE SODIUM; MAGNESIUM STEARATE; POLYVINYL ALCOHOL, UNSPECIFIED; TITANIUM DIOXIDE; POLYETHYLENE GLYCOL 3350; TALC; FERRIC OXIDE YELLOW

HIGHLIGHTS OF PRESCRIBING INFORMATION

These highlights do not include all the information needed to use VEMLIDY safely and effectively. See full prescribing information for VEMLIDY.
VEMLIDY® (tenofovir alafenamide) tablets, for oral use
Initial U.S. Approval: 2015

WARNING: POSTTREATMENT SEVERE ACUTE EXACERBATION OF HEPATITIS B

See full prescribing information for complete boxed warning.

Discontinuation of anti-hepatitis B therapy may result in severe acute exacerbations of hepatitis B. Hepatic function should be monitored closely in patients who discontinue VEMLIDY. If appropriate, resumption of anti-hepatitis B therapy may be warranted. (5.1)

RECENT MAJOR CHANGES

Indications and Usage (1) | 03/2024
Dosage and Administration: Recommended Dosage in Adults and Pediatric Patients 6 Years of Age and Older and Weighing at Least 25 kg (2.2) | 03/2024

1 INDICATIONS AND USAGE

VEMLIDY is a hepatitis B virus (HBV) nucleoside analog reverse transcriptase inhibitor and is indicated for the treatment of chronic hepatitis B virus infection in adults and pediatric patients 6 years of age and older and weighing at least 25 kg with compensated liver disease. (1)

2 DOSAGE AND ADMINISTRATION

- Testing: Prior to initiation of VEMLIDY, test patients for HIV infection. VEMLIDY alone should not be used in patients with HIV infection. Prior to or when initiating VEMLIDY, and during treatment on a clinically appropriate schedule, assess serum creatinine, estimated creatinine clearance, urine glucose, and urine protein in all patients. Also assess serum phosphorus in patients with chronic kidney disease. (2.1)
- Recommended dosage: 25 mg (one tablet) taken orally once daily with food. (2.2)
- Renal Impairment: VEMLIDY is not recommended in patients with estimated creatinine clearance below 15 mL per minute who are not receiving chronic hemodialysis. In patients on chronic hemodialysis, on hemodialysis days, administer VEMLIDY after hemodialysis. (2.3)
- Hepatic Impairment: VEMLIDY is not recommended in patients with decompensated (Child-Pugh B or C) hepatic impairment. (2.4)

3 DOSAGE FORMS AND STRENGTHS

Tablets: 25 mg of tenofovir alafenamide. (3)

4 CONTRAINDICATIONS

None. (4)

5 WARNINGS AND PRECAUTIONS

- HBV and HIV-1 coinfection: VEMLIDY alone is not recommended for the treatment of HIV-1 infection. HIV-1 resistance may develop in these patients. (5.2)
- New onset or worsening renal impairment: Prior to or when initiating VEMLIDY, and during treatment on a clinically appropriate schedule, assess serum creatinine, estimated creatinine clearance, urine glucose, and urine protein in all patients. Also assess serum phosphorus in patients with chronic kidney disease. (5.3)
- Lactic acidosis/severe hepatomegaly with steatosis: Discontinue treatment in patients who develop symptoms or laboratory findings suggestive of lactic acidosis or pronounced hepatotoxicity. (5.4)

6 ADVERSE REACTIONS

Most common adverse reaction (incidence greater than or equal to 10%, all grades) is headache. (6.1)

To report SUSPECTED ADVERSE REACTIONS, contact Gilead Sciences, Inc. at 1-800-GILEAD-5 or FDA at 1-800-FDA-1088 or www.fda.gov/medwatch.

7 DRUG INTERACTIONS

VEMLIDY is a substrate of P-glycoprotein (P-gp) and BCRP. Drugs that strongly affect P-gp and BCRP activity may lead to changes in VEMLIDY absorption. Consult the full prescribing information prior to and during treatment for potential drug-drug interactions. (7)

FULL PRESCRIBING INFORMATION

WARNING: POSTTREATMENT SEVERE ACUTE EXACERBATION OF HEPATITIS B

Discontinuation of anti-hepatitis B therapy, including VEMLIDY, may result in severe acute exacerbations of hepatitis B. Hepatic function should be monitored closely with both clinical and laboratory follow-up for at least several months in patients who discontinue anti-hepatitis B therapy, including VEMLIDY. If appropriate, resumption of anti-hepatitis B therapy may be warranted [see Warnings and Precautions (5.1)].

1 INDICATIONS AND USAGE

VEMLIDY is indicated for the treatment of chronic hepatitis B virus (HBV) infection in adults and pediatric patients 6 years of age and older and weighing at least 25 kg with compensated liver disease [see Clinical Studies (14)].

2 DOSAGE AND ADMINISTRATION

2.1 Testing Prior to Initiation of VEMLIDY

Prior to initiation of VEMLIDY, patients should be tested for HIV-1 infection. VEMLIDY alone should not be used in patients with HIV-1 infection [see Warnings and Precautions (5.2)].

Prior to or when initiating VEMLIDY, and during treatment with VEMLIDY on a clinically appropriate schedule, assess serum creatinine, estimated creatinine clearance, urine glucose, and urine protein in all patients. In patients with chronic kidney disease, also assess serum phosphorus [see Warnings and Precautions (5.3)].

2.2 Recommended Dosage in Adults and Pediatric Patients 6 Years of Age and Older and Weighing at Least 25 kg

The recommended dosage of VEMLIDY in adults and pediatric patients 6 years of age and older and weighing at least 25 kg is one 25 mg tablet taken orally once daily with food [see Clinical Pharmacology (12.3)].

2.3 Dosage in Patients with Renal Impairment

No dosage adjustment of VEMLIDY is required in patients with estimated creatinine clearance greater than or equal to 15 mL per minute, or in patients with end stage renal disease (ESRD; estimated creatinine clearance below 15 mL per minute) who are receiving chronic hemodialysis. On days of hemodialysis, administer VEMLIDY after completion of hemodialysis treatment.

VEMLIDY is not recommended in patients with ESRD who are not receiving chronic hemodialysis [see Use in Specific Populations (8.6) and Clinical Pharmacology (12.3)].

No data are available to make dose recommendations in pediatric patients with renal impairment.

2.4 Dosage in Patients with Hepatic Impairment

No dosage adjustment of VEMLIDY is required in patients with mild hepatic impairment (Child-Pugh A). VEMLIDY is not recommended in patients with decompensated (Child-Pugh B or C) hepatic impairment [see Use in Specific Populations (8.7) and Clinical Pharmacology (12.3)].

3 DOSAGE FORMS AND STRENGTHS

Tablets: 25 mg of tenofovir alafenamide (equivalent to 28 mg of tenofovir alafenamide fumarate) — yellow, round, film-coated tablets, debossed with "GSI" on one side of the tablet and "25" on the other side.

4 CONTRAINDICATIONS

None.

5 WARNINGS AND PRECAUTIONS

5.1 Severe Acute Exacerbation of Hepatitis B after Discontinuation of Treatment

Discontinuation of anti-hepatitis B therapy, including VEMLIDY, may result in severe acute exacerbations of hepatitis B. Patients who discontinue VEMLIDY should be closely monitored with both clinical and laboratory follow-up for at least several months after stopping treatment. If appropriate, resumption of anti-hepatitis B therapy may be warranted.

5.2 Risk of Development of HIV-1 Resistance in Patients Coinfected with HBV and HIV-1

Due to the risk of development of HIV-1 resistance, VEMLIDY alone is not recommended for the treatment of HIV-1 infection. The safety and efficacy of VEMLIDY have not been established in patients coinfected with HBV and HIV-1. HIV antibody testing should be offered to all HBV-infected patients before initiating therapy with VEMLIDY, and, if positive, an appropriate antiretroviral combination regimen that is recommended for patients coinfected with HIV-1 should be used.

5.3 New Onset or Worsening Renal Impairment

Postmarketing cases of renal impairment, including acute renal failure, proximal renal tubulopathy (PRT), and Fanconi syndrome have been reported with TAF-containing products; while most of these cases were characterized by potential confounders that may have contributed to the reported renal events, it is also possible these factors may have predisposed patients to tenofovir-related adverse events [see Adverse Reactions (6.2)].

Patients taking tenofovir prodrugs who have impaired renal function and those taking nephrotoxic agents, including non-steroidal anti-inflammatory drugs, are at increased risk of developing renal-related adverse reactions [see Drug Interactions (7.2)].

Prior to or when initiating VEMLIDY, and during treatment with VEMLIDY on a clinically appropriate schedule, assess serum creatinine, estimated creatinine clearance, urine glucose, and urine protein in all patients. In patients with chronic kidney disease, also assess serum phosphorus. Discontinue VEMLIDY in patients who develop clinically significant decreases in renal function or evidence of Fanconi syndrome [see Adverse Reactions (6.1) and Use in Specific Populations (8.6)].

5.4 Lactic Acidosis/Severe Hepatomegaly with Steatosis

Lactic acidosis and severe hepatomegaly with steatosis, including fatal cases, have been reported with the use of nucleoside analogs, including tenofovir disoproxil fumarate (TDF), another prodrug of tenofovir, alone or in combination with other antiretrovirals. Treatment with VEMLIDY should be suspended in any patient who develops clinical or laboratory findings suggestive of lactic acidosis or pronounced hepatotoxicity (which may include hepatomegaly and steatosis even in the absence of marked transaminase elevations).

6 ADVERSE REACTIONS

The following adverse reactions are discussed in other sections of the labeling:

- Severe Acute Exacerbation of Hepatitis B [see Warnings and Precautions (5.1)]
- New Onset or Worsening of Renal Impairment [see Warnings and Precautions (5.3)]
- Lactic Acidosis/Severe Hepatomegaly with Steatosis [see Warnings and Precautions (5.4)]

6.1 Clinical Trials Experience

Because clinical trials are conducted under widely varying conditions, adverse reaction rates observed in the clinical trials of a drug cannot be directly compared to rates in the clinical trials of another drug and may not reflect the rates observed in practice.

Adverse Reactions in Adult Subjects with Chronic Hepatitis B and Compensated Liver Disease

The safety assessment of VEMLIDY was based on pooled data through the Week 96 data analysis from 1298 subjects in two randomized, double-blind, active-controlled trials, Trial 108 and Trial 110, in adult subjects with chronic hepatitis B and compensated liver disease. A total of 866 subjects received VEMLIDY 25 mg once daily [see Clinical Studies (14.2)]. Further safety assessment was based on pooled data from Trials 108 and 110 from subjects who continued to receive their original blinded treatment through Week 120 and additionally from subjects who received open-label VEMLIDY from Week 96 through Week 120 (n = 361 remained on VEMLIDY; n = 180 switched from TDF to VEMLIDY at Week 96).

Based on the Week 96 analysis, the most common adverse reaction (all Grades) reported in at least 10% of subjects in the VEMLIDY group was headache. The proportion of subjects who discontinued treatment with VEMLIDY or TDF due to adverse reactions of any severity was 1.5% and 0.9%, respectively. Table 1 displays the frequency of the adverse reactions (all Grades) greater than or equal to 5% in the VEMLIDY group.

Table 1 Adverse Reactions [Frequencies of adverse reactions are based on all treatment-emergent adverse events, regardless of relationship to study drug.] (All Grades) Reported in ≥5% of Subjects with Chronic HBV Infection and Compensated Liver Disease in Trials 108 and 110 (Week 96 analysis [Double-blind phase.])
 | VEMLIDY (N=866) | TDF (N=432)
Headache | 12% | 10%
Abdominal pain [Grouped term including abdominal pain upper, abdominal pain, abdominal pain lower, and abdominal tenderness.] | 9% | 6%
Cough | 8% | 8%
Back pain | 6% | 6%
Fatigue | 6% | 5%
Nausea | 6% | 6%
Arthralgia | 5% | 6%
Diarrhea | 5% | 5%
Dyspepsia | 5% | 5%

Additional adverse reactions occurring in less than 5% of subjects in Trials 108 and 110 included vomiting, rash, and flatulence.

The safety profile of VEMLIDY in subjects who continued to receive blinded treatment through Week 120 was similar to that at Week 96. The safety profile of VEMLIDY in subjects who remained on VEMLIDY in the open-label phase through Week 120 was similar to that in subjects who switched from TDF to VEMLIDY at Week 96.

Renal Laboratory Tests

In a pooled analysis of Trials 108 and 110 in adult subjects with chronic hepatitis B and a median baseline estimated creatinine clearance between 106 and 105 mL per minute (for the VEMLIDY and TDF groups, respectively), mean serum creatinine increased by less than 0.1 mg/dL and median serum phosphorus decreased by 0.1 mg/dL in both treatment groups at Week 96. Median change from baseline to Week 96 in estimated creatinine clearance was -1.2 mL per minute in the VEMLIDY group and -4.8 mL per minute in those receiving TDF.

In subjects who remained on blinded treatment beyond Week 96 in Trials 108 and 110, change from baseline in renal laboratory parameter values in each group at Week 120 were similar to those at Week 96. In the open-label phase, median change in estimated creatinine clearance by Cockcroft-Gault method from Week 96 to Week 120 was -0.6 mL per minute in subjects who remained on VEMLIDY and +1.8 mL per minute in those who switched from TDF to VEMLIDY at Week 96. Mean serum creatinine and median serum phosphorus values at Week 120 were similar to those at Week 96 in subjects who remained on VEMLIDY and in subjects who switched from TDF to VEMLIDY.

The long-term clinical significance of these renal laboratory changes on adverse reaction frequencies between VEMLIDY and TDF is not known.

Bone Mineral Density Effects

In a pooled analysis of Trials 108 and 110, the mean percentage change in bone mineral density (BMD) from baseline to Week 96 as assessed by dual-energy X-ray absorptiometry (DXA) was -0.7% with VEMLIDY compared to -2.6% with TDF at the lumbar spine and -0.3% compared to -2.5% at the total hip. BMD declines of 5% or greater at the lumbar spine were experienced by 11% of VEMLIDY subjects and 25% of TDF subjects at Week 96. BMD declines of 7% or greater at the femoral neck were experienced by 5% of VEMLIDY subjects and 13% of TDF subjects at Week 96.

In subjects who remained on blinded treatment beyond Week 96 in Trials 108 and 110, mean percentage change in BMD in each group at Week 120 was similar to that at Week 96. In the open-label phase, mean percentage change in BMD from Week 96 to Week 120 in subjects who remained on VEMLIDY was 0.6% at the lumbar spine and 0% at the total hip, compared to 1.7% at the lumbar spine and 0.6% at the total hip in those who switched from TDF to VEMLIDY.

The long-term clinical significance of these BMD changes is not known.

Laboratory Abnormalities

The frequency of laboratory abnormalities (Grades 3–4) occurring in at least 2% of subjects receiving VEMLIDY in Trials 108 and 110 are presented in Table 2.

Table 2 Laboratory Abnormalities (Grades 3–4) Reported in ≥2% of Subjects with Chronic HBV Infection and Compensated Liver Disease in Trials 108 and 110 (Week 96 analysis [Double-blind phase.])
Laboratory Parameter Abnormality [Frequencies are based on treatment-emergent laboratory abnormalities.] | VEMLIDY (N=866) | TDF (N=432)
ALT (>5 × ULN) | 8% | 10%
LDL-cholesterol (fasted) (>190 mg/dL) | 6% | 1%
Glycosuria (≥3+) | 5% | 2%
AST (>5 × ULN) | 3% | 5%
Creatine Kinase (≥10 × ULN) | 3% | 3%
Serum Amylase (>2.0 × ULN) | 3% | 3%
ULN=Upper Limit of Normal

The overall incidence of blinded treatment ALT flares (defined as confirmed serum ALT greater than 2 × baseline and greater than 10 × ULN at 2 consecutive postbaseline visits, with or without associated symptoms) was similar between VEMLIDY (0.6%) and TDF (0.9%) through Week 96. ALT flares generally were not associated with coincident elevations in bilirubin, occurred within the first 12 weeks of treatment, and resolved without recurrence.

Based on the Week 120 analysis, the frequencies of lab abnormalities in subjects who remained on VEMLIDY in the open-label phase were similar to those in subjects who switched from TDF to VEMLIDY at Week 96.

Amylase and Lipase Elevations and Pancreatitis

At Week 96, in Trials 108 and 110, eight subjects treated with VEMLIDY with elevated amylase levels had associated symptoms, such as nausea, low back pain; abdominal tenderness, pain, and distension; and biliary pancreatitis and pancreatitis. Of these eight, two subjects discontinued VEMLIDY due to elevated amylase and/or lipase; one subject experienced recurrence of adverse events when VEMLIDY was restarted. No subject treated with TDF had associated symptoms or discontinued treatment.

From Week 96 to Week 120, one additional subject who continued open-label VEMLIDY and none of the subjects who switched from TDF to VEMLIDY had elevated amylase levels and associated symptoms.

Serum Lipids

Changes from baseline in total cholesterol, HDL-cholesterol, LDL-cholesterol, triglycerides, and total cholesterol to HDL ratio among subjects treated with VEMLIDY and TDF in Trials 108 and 110 are presented in Table 3.

Table 3 Lipid Abnormalities: Mean Change from Baseline in Lipid Parameters in Patients with Chronic HBV Infection and Compensated Liver Disease in Trials 108 and 110 (Week 96 analysis)
 | VEMLIDY (N=866) |  | TDF (N=432)
 | Baseline | Week 96 | Baseline | Week 96
 | mg/dL | Change [The change from baseline is the mean of within-subject changes from baseline for subjects with both baseline and Week 96 values.] | mg/dL | Change
Total Cholesterol (fasted) | 188 [n=835] | -1 [n=742] | 193 [n=423] | -25 [n=368]
HDL-Cholesterol (fasted) | 60 [n=835] | -5 [n=740] | 61 [n=423] | -12 [n=368]
LDL-Cholesterol (fasted) | 116 [n=835] | +7 [n=741] | 120 [n=423] | -10 [n=368]
Triglycerides (fasted) | 102 [n=836] | +13 [n=743] | 102 [n=423] | -7 [n=368]
Total Cholesterol to HDL ratio | 3 [n=835] | 0 [n=740] | 3 [n=423] | 0 [n=368]

In the open-label phase, lipid parameters at Week 120 in subjects who remained on VEMLIDY were similar to those at Week 96. In subjects who switched from TDF to VEMLIDY, mean change from Week 96 to Week 120 in total cholesterol was 23 mg/dL, HDL-cholesterol was 5 mg/dL, LDL-cholesterol was 16 mg/dL, triglycerides was 30 mg/dL, and total cholesterol to HDL ratio was 0 mg/dL.

Adverse Reactions in Virologically Suppressed Adult Subjects with Chronic Hepatitis B

The safety of VEMLIDY in virologically suppressed adults is based on Week 48 data from a randomized, double-blind, active-controlled trial (Trial 4018) in which subjects taking TDF at baseline were randomized to switch to VEMLIDY (N=243) or to continue their TDF treatment (N=245). Adverse reactions observed with VEMLIDY in Trial 4018 were similar to those in Trials 108 and 110 [see Clinical Studies (14.3)].

Renal Laboratory Tests, Bone Mineral Density Effects, and Serum Lipids

In virologically suppressed adults in Trial 4018, changes from baseline in renal function, BMD, and lipid parameters in the VEMLIDY and TDF groups at Week 48 were similar to those observed in Trials 108 and 110 at Week 96.

Adverse Reactions in Adult Subjects with Chronic Hepatitis B and Renal Impairment

In an open-label trial (Trial 4035) in virologically suppressed adult subjects with chronic hepatitis B switching to VEMLIDY 25 mg, the safety of VEMLIDY was assessed in 78 subjects with moderate to severe renal impairment (estimated creatinine clearance between 15 and 59 mL per minute by Cockcroft-Gault method; Part A, Cohort 1) and 15 subjects with ESRD (estimated creatinine clearance below 15 mL per minute) receiving chronic hemodialysis (Part A, Cohort 2). The safety of VEMLIDY, including changes from baseline in renal function, BMD, and lipid parameters, was similar to that observed in clinical trials of VEMLIDY in subjects with compensated liver disease but without renal impairment [see Use in Specific Populations (8.6) and Clinical Studies (14.4)].

Adverse Reactions in Pediatric Subjects with Chronic Hepatitis B

The safety of VEMLIDY was evaluated in HBV-infected treatment-naïve and treatment-experienced pediatric subjects between the ages of 12 to less than 18 years and weighing at least 35 kg (Cohort 1; N=70) and 6 to less than 12 years and weighing at least 25 kg (Cohort 2, Group 1: N=18) through Week 24 in a randomized, double-blind, placebo-controlled clinical trial (Trial 1092). Subjects were then eligible to roll over to receive open-label VEMLIDY. Safety data are available through Week 96 [see Clinical Studies (14.5)]. The safety profile of VEMLIDY was similar to that in adults.

Bone Mineral Density Effects

Among the Cohort 1 and Cohort 2, Group 1 subjects treated with VEMLIDY and placebo, the mean percent change in BMD from baseline to Week 24 was 1.6% (N=48) and 1.9% (N=23) for lumbar spine, and 1.9% (N=50) and 2.0% (N=23) for whole body, respectively. At Week 24, mean changes from baseline BMD Z-scores were 0.01 and -0.07 for lumbar spine, and -0.04 and -0.04 for whole body, for the VEMLIDY and placebo groups, respectively. At Week 24, BMD declines of 4% or greater at lumbar spine and whole body were experienced by 6% and 2% of VEMLIDY subjects, respectively.

In the open-label phase, mean percentage change in lumbar spine and whole body BMD and BMD Z-scores from baseline to Week 96 was similar in subjects who remained on VEMLIDY compared to those who switched from placebo to VEMLIDY.

6.2 Postmarketing Experience

The following adverse reactions have been identified during post approval use of VEMLIDY or other products containing tenofovir alafenamide. Because these reactions are reported voluntarily from a population of uncertain size, it is not always possible to reliably estimate their frequency or establish a causal relationship to drug exposure.

Skin and Subcutaneous Tissue Disorders

Angioedema, urticaria

Renal and Urinary Disorders

Acute renal failure, acute tubular necrosis, proximal renal tubulopathy, and Fanconi syndrome

7 DRUG INTERACTIONS

7.1 Potential for Other Drugs to Affect VEMLIDY

VEMLIDY is a substrate of P-glycoprotein (P-gp) and BCRP. Drugs that strongly affect P-gp and BCRP activity may lead to changes in tenofovir alafenamide absorption (see Table 4). Drugs that induce P-gp activity are expected to decrease the absorption of tenofovir alafenamide, resulting in decreased plasma concentrations of tenofovir alafenamide, which may lead to loss of therapeutic effect of VEMLIDY. Coadministration of VEMLIDY with other drugs that inhibit P-gp and BCRP may increase the absorption and plasma concentration of tenofovir alafenamide.

7.2 Drugs Affecting Renal Function

Because tenofovir is primarily excreted by the kidneys by a combination of glomerular filtration and active tubular secretion, coadministration of VEMLIDY with drugs that reduce renal function or compete for active tubular secretion may increase concentrations of tenofovir and other renally eliminated drugs and this may increase the risk of adverse reactions. Some examples of drugs that are eliminated by active tubular secretion include, but are not limited to, acyclovir, cidofovir, ganciclovir, valacyclovir, valganciclovir, aminoglycosides (e.g., gentamicin), and high-dose or multiple NSAIDs [see Warnings and Precautions (5.3)].

7.3 Established and Other Potentially Significant Interactions

Table 4 provides a listing of established or potentially clinically significant drug interactions. The drug interactions described are based on studies conducted with tenofovir alafenamide or are predicted drug interactions that may occur with VEMLIDY [For magnitude of interaction, see Clinical Pharmacology (12.3)]. Information regarding potential drug-drug interactions with HIV antiretrovirals is not provided (see the prescribing information for emtricitabine/tenofovir alafenamide for interactions with HIV antiretrovirals). The table includes potentially significant interactions but is not all inclusive.

Table 4 Established and Other Potentially Significant Drug Interactions [This table is not all inclusive.]
Concomitant Drug Class: Drug Name | Effect on Concentration [↓ = decrease.] | Clinical Comment
Anticonvulsants: | ↓ tenofovir alafenamide | When coadministered with carbamazepine, the tenofovir alafenamide dose should be increased to two tablets once daily. Coadministration of VEMLIDY with oxcarbazepine, phenobarbital, or phenytoin is not recommended.
Carbamazepine [Indicates that a drug interaction study was conducted.] [P-gp inducer] | ↓ tenofovir alafenamide | When coadministered with carbamazepine, the tenofovir alafenamide dose should be increased to two tablets once daily. Coadministration of VEMLIDY with oxcarbazepine, phenobarbital, or phenytoin is not recommended.
Oxcarbazepine | ↓ tenofovir alafenamide | When coadministered with carbamazepine, the tenofovir alafenamide dose should be increased to two tablets once daily. Coadministration of VEMLIDY with oxcarbazepine, phenobarbital, or phenytoin is not recommended.
Phenobarbital | ↓ tenofovir alafenamide | When coadministered with carbamazepine, the tenofovir alafenamide dose should be increased to two tablets once daily. Coadministration of VEMLIDY with oxcarbazepine, phenobarbital, or phenytoin is not recommended.
Phenytoin | ↓ tenofovir alafenamide | When coadministered with carbamazepine, the tenofovir alafenamide dose should be increased to two tablets once daily. Coadministration of VEMLIDY with oxcarbazepine, phenobarbital, or phenytoin is not recommended.
Antimycobacterials: | ↓ tenofovir alafenamide | Coadministration of VEMLIDY with rifabutin, rifampin or rifapentine is not recommended.
Rifabutin | ↓ tenofovir alafenamide | Coadministration of VEMLIDY with rifabutin, rifampin or rifapentine is not recommended.
Rifampin | ↓ tenofovir alafenamide | Coadministration of VEMLIDY with rifabutin, rifampin or rifapentine is not recommended.
Rifapentine | ↓ tenofovir alafenamide | Coadministration of VEMLIDY with rifabutin, rifampin or rifapentine is not recommended.
Herbal Products: | ↓ tenofovir alafenamide | Coadministration of VEMLIDY with St. John's wort is not recommended.
St. John's wort (Hypericum perforatum) | ↓ tenofovir alafenamide | Coadministration of VEMLIDY with St. John's wort is not recommended.

7.4 Drugs without Clinically Significant Interactions with VEMLIDY

Based on drug interaction studies conducted with VEMLIDY, no clinically significant drug interactions have been observed with: ethinyl estradiol, ledipasvir/sofosbuvir, midazolam, norgestimate, sertraline, sofosbuvir, sofosbuvir/velpatasvir, and sofosbuvir/velpatasvir/voxilaprevir.

8 USE IN SPECIFIC POPULATIONS

8.1 Pregnancy

Pregnancy Exposure Registry

There is a pregnancy exposure registry that monitors pregnancy outcomes in women exposed to VEMLIDY during pregnancy. Healthcare providers are encouraged to register patients by calling the Antiretroviral Pregnancy Registry (APR) at 1-800-258-4263.

Risk Summary

Available data from the APR show no statistically significant difference in the overall risk of birth defects for tenofovir alafenamide (TAF) compared with the background rate for major birth defects of 2.7% in the U.S. reference population of the Metropolitan Atlanta Congenital Defects Program (MACDP) (see Data). The rate of miscarriage is not reported in the APR. The estimated background rate of miscarriage in clinically recognized pregnancies in the U.S. general population is 15% to 20%.

In animal studies, no adverse developmental effects were observed when tenofovir alafenamide was administered during the period of organogenesis at exposure equal to or 51 times (rats and rabbits, respectively) the tenofovir alafenamide exposure at the recommended daily dose of VEMLIDY (see Data). No adverse effects were observed in the offspring when TDF was administered through lactation at tenofovir exposures of approximately 12 times the exposure at the recommended daily dosage of VEMLIDY.

Data

Human Data

Based on prospective reports to the APR of over 1330 exposures to TAF-containing regimens during pregnancy resulting in live births (including over 1080 exposed in the first trimester and over 240 exposed in the second/third trimester), the prevalence of birth defects in live births was 3.9% (95% CI: 2.8% to 5.2%) and 4.8% (95% CI: 2.5% to 8.3%) following first and second/third trimester exposure, respectively, to TAF-containing regimens. Methodologic limitations of the APR include the use of MACDP as the external comparator group. The MACDP population is not disease-specific, evaluates women and infants from a limited geographic area, and does not include outcomes for births that occurred at less than 20 weeks gestation.

Animal Data

Embryonic fetal development studies performed in rats and rabbits revealed no evidence of impaired fertility or harm to the fetus. The embryo-fetal NOAELs (no observed adverse effect level) in rats and rabbits occurred at tenofovir alafenamide exposures similar to and 51 times higher than, respectively, the exposure in humans at the recommended daily dose. Tenofovir alafenamide is rapidly converted to tenofovir; the observed tenofovir exposure in rats and rabbits were 54 (rats) and 85 (rabbits) times higher than human tenofovir exposures at the recommended daily dose.

Tenofovir alafenamide was administered orally to pregnant rats (25, 100, or 250 mg/kg/day) and rabbits (10, 30, or 100 mg/kg/day) through organogenesis (on gestation days 6 through 17, and 7 through 20, respectively). No adverse embryo-fetal effects were observed in rats and rabbits at tenofovir alafenamide exposures approximately similar to (rats) and 51 (rabbits) times higher than the exposure in humans at the recommended daily dose of VEMLIDY. Tenofovir alafenamide is rapidly converted to tenofovir; the observed tenofovir exposures in rats and rabbits were 54 (rats) and 85 (rabbits) times higher than human tenofovir exposures at the recommended daily dose. Since tenofovir alafenamide is rapidly converted to tenofovir and a lower tenofovir exposure in rats and mice was observed after tenofovir alafenamide administration compared to TDF, another prodrug for tenofovir administration, a pre/postnatal development study in rats was conducted only with TDF. Doses up to 600 mg/kg/day were administered through lactation; no adverse effects were observed in the offspring on gestation day 7 [and lactation day 20] at tenofovir exposures of approximately 12 [18] times higher than the exposures in humans at the recommended daily dose of VEMLIDY.

8.2 Lactation

Risk Summary

Data from the published literature report the presence of TAF and tenofovir in human milk. Data from the published literature have not reported adverse effects of TAF on a breastfed child. There are no data on the effects of TAF on milk production.

The developmental and health benefits of breastfeeding should be considered along with the mother's clinical need for VEMLIDY and any potential adverse effects on the breastfed infant from VEMLIDY or from the underlying maternal condition.

8.4 Pediatric Use

The pharmacokinetics, safety, and effectiveness of VEMLIDY for the treatment of chronic HBV infection have been established in pediatric patients between the ages of 6 to less than 18 years and weighing at least 25 kg (N=59) in Trial 1092 up to 96 weeks. No clinically meaningful differences in pharmacokinetics or safety were observed in comparison to those observed in adults [see Adverse Reactions (6.1), Clinical Pharmacology (12.3), and Clinical Studies (14.5)].

Safety and effectiveness of VEMLIDY has not been established in pediatric patients with chronic HBV infection who are less than 6 years of age or weigh less than 25 kg.

8.5 Geriatric Use

In clinical trials, VEMLIDY was administered to 89 subjects aged 65 and over. No clinically significant differences in safety or efficacy have been observed between elderly subjects and subjects between 18 and less than 65 years of age.

8.6 Renal Impairment

No dosage adjustment of VEMLIDY is required in patients with mild, moderate, or severe renal impairment, or in patients with ESRD (estimated creatinine clearance below 15 mL per minute) who are receiving chronic hemodialysis. On days of hemodialysis, administer VEMLIDY after completion of hemodialysis treatment [see Dosage and Administration (2.3)].

The safety and efficacy of VEMLIDY in HBV-infected adult subjects with moderate to severe renal impairment (estimated creatinine clearance between 15 and 59 mL per minute by Cockcroft-Gault method) and ESRD (estimated creatinine clearance of less than 15 mL per minute by Cockcroft-Gault method) receiving chronic hemodialysis were evaluated in 78 and 15 subjects, respectively, in an open-label trial (Trial 4035, Part A). Overall, 98% of subjects achieved HBV DNA <20 IU/mL at Week 24 (Cohort 1, 97%; Cohort 2, 100%) and the safety of VEMLIDY was similar to that observed in clinical trials of VEMLIDY in subjects with compensated liver disease but without renal impairment [see Adverse Reactions (6.1) and Clinical Studies (14.4)].

The safety and efficacy of elvitegravir/cobicistat/emtricitabine/tenofovir alafenamide 150/150/200/10 mg was previously evaluated in 55 virologically suppressed HIV-1 infected subjects with ESRD receiving chronic hemodialysis in an open-label trial (Trial 1825). Tenofovir alafenamide exposures are similar when comparing tenofovir alafenamide 25 mg and tenofovir alafenamide 10 mg as part of elvitegravir/cobicistat/emtricitabine/tenofovir alafenamide.

Among subjects with ESRD receiving chronic hemodialysis and administered tenofovir alafenamide, higher exposures of tenofovir were observed in HBV-infected subjects (Trial 4035 Part A) compared to HIV-infected subjects (Trial 1825). The clinical significance of these higher exposures is not established [see Clinical Pharmacology (12.3)].

VEMLIDY is not recommended in patients with ESRD (estimated creatinine clearance below 15 mL per minute by Cockcroft-Gault method) who are not receiving chronic hemodialysis as the safety of VEMLIDY has not been established in this population [see Dosage and Administration (2.3) and Clinical Pharmacology (12.3)].

8.7 Hepatic Impairment

No dosage adjustment of VEMLIDY is required in patients with mild hepatic impairment (Child-Pugh A). The safety and efficacy of VEMLIDY in patients with decompensated cirrhosis (Child-Pugh B or C) have not been established; therefore, VEMLIDY is not recommended in patients with decompensated (Child-Pugh B or C) hepatic impairment [see Dosage and Administration (2.4) and Clinical Pharmacology (12.3)].

10 OVERDOSAGE

If overdose occurs, monitor patient for evidence of toxicity. Treatment of overdosage with VEMLIDY consists of general supportive measures including monitoring of vital signs as well as observation of the clinical status of the patient. Tenofovir is efficiently removed by hemodialysis with an extraction coefficient of approximately 54%.

11 DESCRIPTION

VEMLIDY is a tablet containing tenofovir alafenamide for oral administration. Tenofovir alafenamide, a hepatitis B virus (HBV) nucleoside analog reverse transcriptase inhibitor, is converted in vivo to tenofovir, an acyclic nucleoside phosphonate (nucleotide) analog of adenosine 5′-monophosphate.

Each tablet contains 25 mg of tenofovir alafenamide (equivalent to 28 mg of tenofovir alafenamide fumarate). The tablets include the following inactive ingredients: croscarmellose sodium, lactose monohydrate, magnesium stearate, and microcrystalline cellulose. The tablets are film coated with a coating material containing: iron oxide yellow, polyethylene glycol, polyvinyl alcohol, talc, and titanium dioxide.

The chemical name of tenofovir alafenamide fumarate drug substance is L-alanine, N-[(S)-[[(1R)-2-(6-amino-9H-purin-9-yl)-1-methylethoxy]methyl]phenoxyphosphinyl]-, 1-methylethyl ester, (2E)-2-butenedioate (2:1).

It has an empirical formula of C21H29O5N6P∙½(C4H4O4) and a formula weight of 534.50. It has the following structural formula:

Tenofovir alafenamide fumarate is a white to off-white or tan powder with a solubility of 4.7 mg per mL in water at 20 °C.

12 CLINICAL PHARMACOLOGY

12.1 Mechanism of Action

Tenofovir alafenamide is an antiviral drug against the hepatitis B virus [see Microbiology (12.4)].

12.2 Pharmacodynamics

Cardiac Electrophysiology

In a thorough QT/QTc study in 48 healthy subjects, tenofovir alafenamide at the recommended dose or at a dose 5 times the recommended dose did not affect the QT/QTc interval and did not prolong the PR interval.

12.3 Pharmacokinetics

The pharmacokinetic properties of VEMLIDY are provided in Table 5. The multiple dose PK parameters of tenofovir alafenamide and its metabolite tenofovir are provided in Table 6.

Table 5 Pharmacokinetic Properties of VEMLIDY
 | Tenofovir Alafenamide
Absorption
Tmax (h) | 0.48
Effect of high fat meal (relative to fasting): AUClast Ratio [Values refer to geometric mean ratio in AUClast [fed/fasted] and (90% confidence interval). High fat meal = ~800 kcal, 50% fat.] | 1.65 (1.51, 1.81)
Distribution
% Bound to human plasma proteins | 80%
Source of protein binding data | Ex vivo
Blood-to-plasma ratio | 1.0
Metabolism
Metabolism [In vivo, TAF is hydrolyzed within cells to form tenofovir (major metabolite), which is phosphorylated to the active metabolite, tenofovir diphosphate. In vitro studies have shown that TAF is metabolized to tenofovir by CES1 in hepatocytes, and by cathepsin A in PBMCs and macrophages.] | CES1 (hepatocytes) Cathepsin A (PBMCs) CYP3A (minimal)
Elimination
Major route of elimination | Metabolism (>80% of oral dose)
t1/2 (h) [t1/2 values refer to median terminal plasma half-life.] | 0.51
% Of dose excreted in urine [Dosing in mass balance study: TAF 25 mg (single dose administration of [^14C] TAF).] | <1
% Of dose excreted in feces | 31.7
CES1 = carboxylesterase 1; PBMCs = peripheral blood mononuclear cells.

Table 6 Multiple Dose PK Parameters of Tenofovir Alafenamide and its Metabolite Tenofovir Following Oral Administration in Adults with Chronic Hepatitis B
Parameter Mean (CV%) | Tenofovir Alafenamide [From Intensive PK analyses in Trial 108 and Trial 110; N = 8.] | Tenofovir
Cmax (mcg per mL) | 0.27 (63.3) | 0.03 (24.6)
AUCtau (mcg∙hour per mL) | 0.27 (47.8) | 0.40 (35.2)
Ctrough (mcg per mL) | NA | 0.01 (39.6)
CV = coefficient of variation; NA = not applicable

Specific Populations

Geriatric Patients, Race, and Gender

Limited data in subjects aged 65 years and over suggest a lack of clinically relevant differences in tenofovir alafenamide or tenofovir pharmacokinetics. No clinically relevant differences in tenofovir alafenamide or tenofovir pharmacokinetics due to race or gender have been identified [see Use in Specific Populations (8.5)].

Pediatric Patients

Steady-state pharmacokinetics of tenofovir alafenamide and its metabolite tenofovir were evaluated in HBV-infected pediatric subjects aged 6 to less than 18 years (Table 7).

Table 7 Multiple Dose PK Parameters of Tenofovir Alafenamide and Tenofovir Following Oral Administration of VEMLIDY 25 mg in HBV-Infected Pediatric Subjects Aged 6 to less than 18 Years
Age Group | Parameter Mean (CV%) | Tenofovir Alafenamide [From Intensive PK analyses in Trial 1092: Cohort 1, N=13 except N=11 for AUCtau; Cohort 2, Group 1, N=5.] | Tenofovir [From Intensive PK analyses in Trial 1092: Cohort 1, N=13; Cohort 2, Group 1, N=5.]
12 to <18 Years weighing ≥35 kg | Cmax (mcg per mL) | 0.188 (45.0) | 0.015 (23.5)
12 to <18 Years weighing ≥35 kg | AUCtau (mcg∙hour per mL) | 0.254 (36.4) | 0.244 (28.3)
12 to <18 Years weighing ≥35 kg | Ctrough (mcg per mL) | NA | 0.0079 (35.0)
6 to <12 Years weighing ≥25 kg | Cmax (mcg per mL) | 0.388 (96.9) | 0.017 (19.6)
6 to <12 Years weighing ≥25 kg | AUCtau (mcg∙hour per mL) | 0.313 (64.8) | 0.272 (17.5)
6 to <12 Years weighing ≥25 kg | Ctrough (mcg per mL) | NA | 0.0089 (10.2)
CV = coefficient of variation; NA = not applicable

Patients with Renal Impairment

In a Phase 1, open-label study, tenofovir alafenamide and tenofovir systemic exposures (AUCinf) were evaluated in subjects with severe renal impairment and in subjects with normal renal function (Table 8). In an open-label trial of elvitegravir/cobicistat/emtricitabine/tenofovir alafenamide 150/150/200/10 mg, tenofovir alafenamide and tenofovir AUC were evaluated in a subset of virologically suppressed HIV-1 infected subjects with ESRD receiving chronic hemodialysis (Table 8). In a Phase 2, open-label trial, tenofovir alafenamide and tenofovir AUC were evaluated in a subset of virologically suppressed HBV-infected subjects with ESRD receiving chronic hemodialysis (Table 8) [see Use in Specific Populations (8.6)]. The pharmacokinetics of tenofovir alafenamide were similar among subjects with normal renal function, subjects with severe renal impairment, and subjects with ESRD receiving chronic hemodialysis. Relative to those with normal renal function, increased tenofovir exposures were observed in subjects with severe renal impairment and subjects with ESRD receiving chronic hemodialysis. Within the chronic hemodialysis population, increased tenofovir exposures were observed in subjects with HBV relative to those with HIV.

Table 8 Pharmacokinetics of Tenofovir Alafenamide and its Metabolite Tenofovir in Subjects with Renal Impairment as Compared to Subjects with Normal Renal Function
Estimated Creatinine Clearance [By Cockcroft-Gault method.] Mean (CV%) | ≥90 mL per minute 25 mg TAF (N=13) [PK assessed on a single dose of TAF 25 mg in subjects with normal renal function and in subjects with severe renal impairment.] | 15–29 mL per minute 25 mg TAF (N=14) | <15 mL per minute 25 mg TAF [PK assessed on the day prior to hemodialysis of TAF 25 mg. These subjects from Trial 4035 had a median baseline eGFR by Cockcroft-Gault of 7.2 mL/min (range, 4.8 to 12.0).] (N=5) | <15 mL per minute 10 mg TAF [Exposures from TAF 25 mg = exposures from TAF 10 mg as part of elvitegravir/cobicistat/emtricitabine/tenofovir alafenamide. PK assessed on the day prior to hemodialysis following 3 consecutive daily doses of elvitegravir/cobicistat/emtricitabine/tenofovir alafenamide. These subjects from Trial 1825 had a median baseline eGFR by Cockcroft-Gault of 10.2 mL/min (range, 6.8 to 19.2) .] (N=12)
Tenofovir alafenamide
AUC (mcg∙hour per mL) | 0.27 (49.2) [AUCinf.] | 0.51 (47.3) | 0.30 (26.7) [AUClast.] | 0.23 (53.2)
Cmax (mcg per mL) | 0.20 (62.1) | 0.36 (65.7) | 0.23 (48.4) | 0.25 (75.4)
Tenofovir
AUC (mcg∙hour per mL) | 0.34 (27.2) | 2.07 (47.1) | 18.8 (30.4) [AUCtau.] | 8.72 (39.4), [N=10.]
Cmax (mcg per mL) | 0.01 (36.5) | 0.03 (32.4) | 0.89 (26.4) | 0.44 (40.9)
C24h (mcg per mL) | 0.004 (25.6) | 0.02 (41.9) | 0.89 (26.4) | 0.26 (73.2)
CV = coefficient of variation

Patients with Hepatic Impairment

Tenofovir alafenamide and tenofovir pharmacokinetics are similar in subjects with mild (Child-Pugh Class A) hepatic impairment and in subjects with normal hepatic function.

HIV and/or Hepatitis C Virus Coinfection

The pharmacokinetics of tenofovir alafenamide have not been fully evaluated in subjects coinfected with HIV and/or hepatitis C virus.

Drug Interaction Studies

[see Drug Interactions (7)]

The effects of coadministered drugs on the exposure of tenofovir alafenamide are shown in Table 9. The effects of tenofovir alafenamide on the exposure of coadministered drugs are shown in Table 10 [For information regarding clinical recommendations, see Drug Interactions (7)]. Information regarding potential drug-drug interactions with HIV antiretrovirals is not provided (see the prescribing information for emtricitabine/tenofovir alafenamide for interactions with HIV antiretrovirals).

Table 9 Drug Interactions: Changes in Pharmacokinetic Parameters for Tenofovir Alafenamide in the Presence of the Coadministered Drug [All interaction studies conducted in healthy subjects.]
Coadministered Drug | Dose of Coadministered Drug (mg) | Tenofovir Alafenamide (mg) | N | Geometric Mean Ratio of TAF Pharmacokinetic Parameters (90% CI) [All no effect boundaries are 70%–143%.] ; No effect = 1.00
Coadministered Drug | Dose of Coadministered Drug (mg) | Tenofovir Alafenamide (mg) | N | Cmax | AUC | Cmin
Carbamazepine | 300 twice daily | 25 once daily [Study conducted with emtricitabine/tenofovir alafenamide.] | 26 | 0.43 (0.36, 0.51) | 0.45 (0.40, 0.51) | NC
Cobicistat [A representative inhibitor of P-glycoprotein.] | 150 once daily | 8 once daily | 12 | 2.83 (2.20, 3.65) | 2.65 (2.29, 3.07) | NC
Ledipasvir/ Sofosbuvir | 90/400 once daily | 25 once daily [Study conducted with emtricitabine/rilpivirine/tenofovir alafenamide.] | 42 | 1.03 (0.94, 1.14) | 1.32 (1.25, 1.40) | NC
Sertraline | 50 single dose | 10 once daily [Study conducted with elvitegravir/cobicistat/emtricitabine/tenofovir alafenamide.] | 19 | 1.00 (0.86, 1.16) | 0.96 (0.89, 1.03) | NC
Sofosbuvir/ Velpatasvir/ Voxilaprevir | 400/100/100+100 voxilaprevir [Study conducted with additional voxilaprevir 100 mg to achieve voxilaprevir exposures expected in HCV-infected patients.] once daily | 25 once daily | 30 | 1.32 (1.17, 1.48) | 1.52 (1.43, 1.61) | NC
NC = not calculated

Table 10 Drug Interactions: Changes in Pharmacokinetic Parameters for Coadministered Drug in the Presence of Tenofovir Alafenamide [All interaction studies conducted in healthy subjects.]
Coadministered Drug | Dose of Coadministered Drug (mg) | Tenofovir Alafenamide (mg) | N | Geometric Mean Ratio of Coadministered Drug Pharmacokinetic Parameters (90% CI) [All no effect boundaries are 70%–143%.] ; No effect = 1.00
Coadministered Drug | Dose of Coadministered Drug (mg) | Tenofovir Alafenamide (mg) | N | Cmax | AUC | Cmin
Ledipasvir | 90 ledipasvir / 400 sofosbuvir once daily | 25 once daily [Study conducted with emtricitabine/rilpivirine/tenofovir alafenamide.] | 41 | 1.01 (0.97, 1.05) | 1.02 (0.97, 1.06) | 1.02 (0.98, 1.07)
Sofosbuvir | 90 ledipasvir / 400 sofosbuvir once daily | 25 once daily [Study conducted with emtricitabine/rilpivirine/tenofovir alafenamide.] | 41 | 0.96 (0.89, 1.04) | 1.05 (1.01, 1.09) | NC
GS-331007 [The predominant circulating nucleoside metabolite of sofosbuvir.] | 90 ledipasvir / 400 sofosbuvir once daily | 25 once daily [Study conducted with emtricitabine/rilpivirine/tenofovir alafenamide.] | 41 | 1.08 (1.05, 1.11) | 1.08 (1.06, 1.10) | 1.10 (1.07, 1.12)
Midazolam [A sensitive CYP3A4 substrate.] | 2.5 single dose orally | 25 once daily | 18 | 1.02 (0.92, 1.13) | 1.13 (1.04, 1.23) | NC
Midazolam [A sensitive CYP3A4 substrate.] | 1 single dose IV | 25 once daily | 18 | 0.99 (0.89, 1.11) | 1.08 (1.04, 1.14) | NC
Norelgestromin | norgestimate 0.180/0.215/0.250 once daily / ethinyl estradiol 0.025 once daily | 25 once daily [Study conducted with emtricitabine/tenofovir alafenamide.] | 29 | 1.17 (1.07, 1.26) | 1.12 (1.07, 1.17) | 1.16 (1.08, 1.24)
Norgestrel | norgestimate 0.180/0.215/0.250 once daily / ethinyl estradiol 0.025 once daily | 25 once daily [Study conducted with emtricitabine/tenofovir alafenamide.] | 29 | 1.10 (1.02, 1.18) | 1.09 (1.01, 1.18) | 1.11 (1.03, 1.20)
Ethinyl estradiol | norgestimate 0.180/0.215/0.250 once daily / ethinyl estradiol 0.025 once daily | 25 once daily [Study conducted with emtricitabine/tenofovir alafenamide.] | 29 | 1.22 (1.15, 1.29) | 1.11 (1.07, 1.16) | 1.02 (0.93, 1.12)
Sertraline | 50 single dose | 10 once daily [Study conducted with elvitegravir/cobicistat/emtricitabine/tenofovir alafenamide.] | 19 | 1.14 (0.94, 1.38) | 0.93 (0.77, 1.13) | NC
Sofosbuvir | 400 once daily | 25 once daily [Study conducted with emtricitabine/rilpivirine/tenofovir alafenamide.] | 30 | 0.95 (0.86, 1.05) | 1.01 (0.97, 1.06) | NC
GS-331007 | 400 once daily | 25 once daily [Study conducted with emtricitabine/rilpivirine/tenofovir alafenamide.] | 30 | 1.02 (0.98, 1.06) | 1.04 (1.01, 1.06) | NC
Velpatasvir | 100 once daily | 25 once daily [Study conducted with emtricitabine/rilpivirine/tenofovir alafenamide.] | 30 | 1.05 (0.96, 1.16) | 1.01 (0.94, 1.07) | 1.01 (0.95, 1.09)
Voxilaprevir | 100+100 [Study conducted with additional voxilaprevir 100 mg to achieve voxilaprevir exposures expected in HCV-infected patients.] once daily | 25 once daily [Study conducted with emtricitabine/rilpivirine/tenofovir alafenamide.] | 30 | 0.96 (0.84, 1.11) | 0.94 (0.84, 1.05) | 1.02 (0.92, 1.12)
NC = not calculated

12.4 Microbiology

Mechanism of Action

Tenofovir alafenamide is a phosphonamidate prodrug of tenofovir (2'-deoxyadenosine monophosphate analog). Tenofovir alafenamide as a lipophilic cell-permeant compound enters primary hepatocytes by passive diffusion and by the hepatic uptake transporters OATP1B1 and OATP1B3. Tenofovir alafenamide is then converted to tenofovir through hydrolysis primarily by carboxylesterase 1 (CES1) in primary hepatocytes. Intracellular tenofovir is subsequently phosphorylated by cellular kinases to the pharmacologically active metabolite tenofovir diphosphate. Tenofovir diphosphate inhibits HBV replication through incorporation into viral DNA by the HBV reverse transcriptase, which results in DNA chain-termination.

Tenofovir diphosphate is a weak inhibitor of mammalian DNA polymerases that include mitochondrial DNA polymerase γ and there is no evidence of toxicity to mitochondria in cell culture.

Antiviral Activity in Cell Culture

The antiviral activity of tenofovir alafenamide was assessed in a transient transfection assay using HepG2 cells against a panel of HBV clinical isolates representing genotypes A-H. The EC50 (50% effective concentration) values for tenofovir alafenamide ranged from 34.7 to 134.4 nM, with an overall mean EC50 value of 86.6 nM. The CC50 (50% cytotoxicity concentration) values in HepG2 cells were greater than 44,400 nM. In cell culture combination antiviral activity studies of tenofovir with the HBV nucleoside reverse transcriptase inhibitors entecavir, lamivudine, and telbivudine, no antagonistic activity was observed.

Resistance in Clinical Trials

Genotypic resistance analysis was performed on paired baseline and on-treatment HBV isolates for subjects who either experienced virologic breakthrough (2 consecutive visits with HBV DNA greater than or equal to 69 IU/mL [400 copies/mL] after having been less than 69 IU/mL, or 1.0-log10 or greater increase in HBV DNA from nadir) through Week 48, or had HBV DNA greater than or equal to 69 IU/mL at early discontinuation at or after Week 24.

In a pooled analysis of treatment-naïve and treatment-experienced subjects receiving VEMLIDY in Trials 108 and 110 [see Clinical Studies (14.2)], treatment-emergent amino acid substitutions in the HBV reverse transcriptase domain, all occurring at polymorphic positions, were observed in some HBV isolates evaluated (5/20); however, no specific substitutions occurred at a sufficient frequency to be associated with resistance to VEMLIDY.

In virologically suppressed subjects receiving VEMLIDY in Trial 4018 [see Clinical Studies (14.3)], no subjects qualified for resistance analysis through 48 weeks of VEMLIDY treatment.

In pediatric Trial 1092, 17/70 subjects in Cohort 1 (aged 12 to less than 18 years) and 7/18 subjects in Cohort 2, Group 1 (aged 6 to less than 12 years) receiving VEMLIDY qualified for resistance analysis at Week 96. Results were obtained from 19/24 qualified subjects. No HBV amino acid substitutions known to be associated with resistance to tenofovir alafenamide were detected through 96 weeks of treatment [see Clinical Studies (14.5)].

Cross-Resistance

The antiviral activity of tenofovir alafenamide was evaluated against a panel of isolates containing substitutions associated with HBV nucleoside reverse transcriptase inhibitor resistance in a transient transfection assay using HepG2 cells. HBV isolates expressing the lamivudine resistance-associated substitutions rtM204V/I (±rtL180M±rtV173L) and expressing the entecavir resistance-associated substitutions rtT184G, rtS202G, or rtM250V in the presence of rtL180M and rtM204V showed less than 2-fold reduced susceptibility (within the inter-assay variability) to tenofovir alafenamide. HBV isolates expressing the rtA181T, rtA181V, or rtN236T single substitutions associated with resistance to adefovir also had less than 2-fold changes in EC50 values; however, the HBV isolate expressing the rtA181V plus rtN236T double substitutions exhibited reduced susceptibility (3.7-fold) to tenofovir alafenamide. The clinical relevance of these substitutions is not known.

13 NONCLINICAL TOXICOLOGY

13.1 Carcinogenesis, Mutagenesis, Impairment of Fertility

Since tenofovir alafenamide is rapidly converted to tenofovir and a lower tenofovir exposure in rats and mice was observed after tenofovir alafenamide administration compared to TDF administration, carcinogenicity studies were conducted only with TDF. Long-term oral carcinogenicity studies of TDF in mice and rats were carried out at exposures up to approximately 10 times (mice) and 4 times (rats) those observed in humans at the 300 mg therapeutic dose of TDF for chronic hepatitis B. The tenofovir exposure in these studies was approximately 151 times (mice) and 50 times (rat) those observed in humans after administration of VEMLIDY treatment. At the high dose in female mice, liver adenomas were increased at tenofovir exposures approximately 151 times those observed after VEMLIDY administration in humans. In rats, the study was negative for carcinogenic findings.

Tenofovir alafenamide was not genotoxic in the reverse mutation bacterial test (Ames test), mouse lymphoma or rat micronucleus assays.

There were no effects on fertility, mating performance or early embryonic development when tenofovir alafenamide was administered to male rats at a dose equivalent to 155 times the human dose based on body surface area comparisons for 28 days prior to mating and to female rats for 14 days prior to mating through Day 7 of gestation.

13.2 Animal Toxicology and/or Pharmacology

Minimal to slight infiltration of mononuclear cells in the posterior uvea was observed in dogs with similar severity after three- and nine-month administration of tenofovir alafenamide; reversibility was seen after a three-month recovery period. At the NOAEL for eye toxicity, the systemic exposure in dogs was 5 (tenofovir alafenamide) and 14 (tenofovir) times the exposure seen in humans at the recommended daily VEMLIDY dosage.

14 CLINICAL STUDIES

14.1 Description of Clinical Trials

The efficacy and safety of VEMLIDY were evaluated in the trials summarized in Table 11.

Table 11 Trials Conducted with VEMLIDY in Subjects with Chronic HBV Infection
Trial | Population | Trial Arms (N) | Primary Endpoint (Week)
Trial 108 [Randomized, double-blind, active controlled trial.] (NCT01940341) | HBeAg-negative TN and TE adults with compensated liver disease | VEMLIDY (285) TDF (140) | 48
Trial 110 (NCT01940471) | HBeAg-positive TN and TE adults with compensated liver disease | VEMLIDY (581) TDF (292) | 48
Trial 4018 (NCT02979613) | HBeAg-negative and HBeAg-positive virologically suppressed [HBV DNA <20 IU/mL at screening.] adults with compensated liver disease | VEMLIDY (243) TDF (245) | 48
Trial 4035 (Part A, Cohort 1) [Open-label trial.] (NCT03180619) | Virologically suppressed adults with moderate to severe renal impairment [Estimated creatinine clearance between 15 and 59 mL per minute by Cockcroft-Gault method.] | VEMLIDY (78) | 24
Trial 4035 (Part A, Cohort 2) (NCT03180619) | Virologically suppressed adults with ESRD [End stage renal disease (estimated creatinine clearance of below 15 mL per minute by Cockcroft-Gault method).] receiving chronic hemodialysis | VEMLIDY (15) | 24
Trial 1092 [Randomized, double-blind, placebo-controlled trial.] (NCT02932150) | Pediatric subjects between the ages of 6 to less than 18 years (at least 25 kg) with compensated liver disease | VEMLIDY (59) Placebo (29) | 24
TE = treatment-experienced, TN = treatment-naive

14.2 Clinical Trials in Adults with Chronic Hepatitis B Virus Infection and Compensated Liver Disease

The efficacy and safety of VEMLIDY in the treatment of adults with chronic hepatitis B virus infection with compensated liver disease are based on 48-week data from two randomized, double-blind, active-controlled trials, Trial 108 (N=425) and Trial 110 (N=873). In both trials, besides trial treatment, subjects were not allowed to receive other nucleosides, nucleotides, or interferon.

In Trial 108, HBeAg-negative treatment-naïve and treatment-experienced subjects with compensated liver disease (no evidence of ascites, hepatic encephalopathy, variceal bleeding, INR <1.5× ULN, total bilirubin <2.5× ULN, and albumin >3.0 mg/dL) were randomized in a 2:1 ratio to receive VEMLIDY 25 mg (N=285) once daily or TDF 300 mg (N=140) once daily for 48 weeks. The mean age was 46 years, 61% were male, 72% were Asian, 25% were White, 2% were Black, and 1% were other races. 24%, 38%, and 31% had HBV genotype B, C, and D, respectively. 21% were treatment experienced [previous treatment with oral antivirals, including entecavir (N=41), lamivudine (N=42), TDF (N=21), or other (N=18)]. At baseline, mean plasma HBV DNA was 5.8 log10 IU/mL, mean serum ALT was 94 U/L, and 9% of subjects had a history of cirrhosis.

In Trial 110, HBeAg-positive treatment-naïve and treatment-experienced subjects with compensated liver disease were randomized in a 2:1 ratio to receive VEMLIDY 25 mg (N=581) once daily or TDF 300 mg (N=292) once daily for 48 weeks. The mean age was 38 years, 64% were male, 82% were Asian, 17% were White, and 1% were Black or other races. 17%, 52%, and 23% had HBV genotype B, C, and D, respectively. 26% were treatment experienced [previous treatment with oral antivirals, including adefovir (N=42), entecavir (N=117), lamivudine (N=84), telbivudine (N=25), TDF (N=70), or other (n=17)]. At baseline, mean plasma HBV DNA was 7.6 log10 IU/mL, mean serum ALT was 120 U/L, and 7% of subjects had a history of cirrhosis.

In both trials, randomization was stratified on prior treatment history (nucleoside naïve or experienced) and baseline HBV DNA (<7, ≥7 to <8, and ≥8 log10 IU/mL in Trial 108; and <8 and ≥8 log10 IU/mL in Trial 110). The efficacy endpoint in both trials was the proportion of subjects with plasma HBV DNA levels below 29 IU/mL at Week 48. Additional efficacy endpoints include the proportion of subjects with ALT normalization, HBsAg loss and seroconversion, and HBeAg loss and seroconversion in Trial 110.

Treatment outcomes of Trials 108 and 110 at Week 48 are presented in Table 12 and Table 13.

Table 12 Trials 108 and 110: HBV DNA Virologic Outcome at Week 48 [Missing = failure analysis.] in Subjects with Chronic HBV Infection and Compensated Liver Disease
 | Trial 108 (HBeAg-Negative) |  | Trial 110 (HBeAg-Positive)
 | VEMLIDY (N=285) | TDF (N=140) | VEMLIDY (N=581) | TDF (N=292)
HBV DNA <29 IU/mL | 94% | 93% | 64% | 67%
Treatment Difference [Adjusted by baseline plasma HBV DNA categories and oral antiviral treatment status strata.] | 1.8% (95% CI = -3.6% to 7.2%) |  | -3.6% (95% CI = -9.8% to 2.6%)
HBV DNA ≥29 IU/mL | 2% | 3% | 31% | 30%
Baseline HBV DNA
<7 log10 IU/mL | 96% (221/230) | 92% (107/116) | N/A | N/A
≥7 log10 IU/mL | 85% (47/55) | 96% (23/24) | N/A | N/A
Baseline HBV DNA
<8 log10 IU/mL | N/A | N/A | 82% (254/309) | 82% (123/150)
≥8 log10 IU/mL |  |  | 43% (117/272) | 51% (72/142)
Nucleoside Naïve [Treatment-naïve subjects received <12 weeks of oral antiviral treatment with any nucleoside or nucleotide analog including TDF or VEMLIDY.] | 94% (212/225) | 93% (102/110) | 68% (302/444) | 70% (156/223)
Nucleoside Experienced | 93% (56/60) | 93% (28/30) | 50% (69/137) | 57% (39/69)
No Virologic Data at Week 48 [Includes subjects who discontinued due to lack of efficacy, adverse event or death, for reasons other than an AE, death or lack or loss of efficacy, e.g., withdrew consent, loss to follow-up, etc., or missing data during Week 48 window but still on study drug.] | 4% | 4% | 5% | 3%

In Trial 108, the proportion of subjects with cirrhosis who achieved HBV DNA <29 IU/mL at Week 48 was 92% (22/24) in the VEMLIDY group and 93% (13/14) in the TDF group. The corresponding proportions in Trial 110 were 63% (26/41) and 67% (16/24) in the VEMLIDY and TDF groups, respectively.

Table 13 Additional Efficacy Parameters at Week 48 [Missing = failure analysis.]
 | Trial 108 (HBeAg-Negative) |  | Trial 110 (HBeAg-Positive)
 | VEMLIDY (N=285) | TDF (N=140) | VEMLIDY (N=581) | TDF (N=292)
ALT Normalized ALT (Central Lab) [The population used for analysis of ALT normalization included only subjects with ALT above upper limit of normal (ULN) of the central laboratory range (>43 U/L for males aged 18 to <69 years and >35 U/L for males ≥69 years; >34 U/L for females 18 to <69 years and >32 U/L for females ≥69 years) at baseline.] | 83% | 75% | 72% | 67%
Normalized ALT (AASLD) [The population used for analysis of ALT normalization included only subjects with ALT above ULN of the 2016 American Association of the Study of Liver Diseases (AASLD) criteria (>30 U/L males and >19 U/L females) at baseline.] | 50% | 32% | 45% | 36%
Serology HBeAg Loss / Seroconversion [The population used for serology analysis included only subjects with antigen (HBeAg) positive and anti-body (HBeAb) negative or missing at baseline.] | N/A | N/A | 14% / 10% | 12% / 8%
HBsAg Loss / Seroconversion | 0 / 0 | 0 / 0 | 1% / 1% | <1% / 0
N/A = not applicable

14.3 Clinical Trials in Virologically Suppressed Adults with Chronic Hepatitis B Virus Infection Who Switched to VEMLIDY

The efficacy and safety of switching from TDF to VEMLIDY in virologically suppressed adults with chronic hepatitis B virus infection is based on 48-week data from a randomized, double-blind, active-controlled trial, Trial 4018 (N=488). Subjects must have been taking TDF 300 mg once daily for at least 12 months, with HBV DNA less than the Lower Limit of Quantitation by local laboratory assessment for at least 12 weeks prior to screening and HBV DNA <20 IU/mL at screening. Subjects were stratified by HBeAg status (HBeAg-positive or HBeAg-negative) and age (≥50 or <50 years) and randomized in a 1:1 ratio to either switch to VEMLIDY 25 mg once daily (N=243) or stay on TDF 300 mg once daily (N=245). The mean age was 51 years (22% were ≥60 years), 71% were male, 82% were Asian, 14% were White, and 68% were HBeAg-negative. At baseline, median duration of prior TDF treatment was 220 and 224 weeks in the VEMLIDY and TDF groups, respectively. At baseline, mean serum ALT was 27 U/L, and 16% of subjects had a history of cirrhosis.

The primary efficacy endpoint was the proportion of subjects with plasma HBV DNA levels ≥20 IU/mL at Week 48. Additional efficacy endpoints in Trial 4018 included the proportion of subjects with HBV DNA <20 IU/mL, ALT normal and normalization, HBsAg loss and seroconversion, and HBeAg loss and seroconversion.

Treatment outcomes of Trial 4018 at Week 48 are presented in Table 14 and Table 15.

Table 14 Trial 4018: HBV DNA Virologic Outcome at Week 48 [Week 48 window was between Day 295 and Day 378 (inclusive).] in Virologically Suppressed Subjects with Chronic HBV Infection
 | VEMLIDY (N=243) | TDF (N=245)
HBV DNA ≥20 IU/mL [No subject discontinued treatment due to lack of efficacy.] | <1% | <1%
Treatment Difference [Adjusted by baseline age groups (< 50, ≥ 50 years) and baseline HBeAg status strata.] | 0.0% (95% CI = -1.9% to 2.0%)
HBV DNA <20 IU/mL | 96% | 96%
Treatment Difference | 0.0% (95% CI = -3.7% to 3.7%)
No Virologic Data at Week 48 | 3% | 3%
Discontinued Study Drug Due to AE or Death and Last Available HBV DNA <20 IU/mL | 1% | 0
Discontinued Study Drug Due to Other Reasons [Includes subjects who discontinued for reasons other than an AE, death, or lack of efficacy, e.g., withdrew consent, loss to follow-up, etc.] and Last Available HBV DNA <20 IU/mL | 2% | 3%

Table 15 Additional Efficacy Parameters at Week 48 [Missing = failure analysis.] (Trial 4018)
 | VEMLIDY (N=243) | TDF (N=245)
ALT
Normal ALT (Central Lab) | 89% | 85%
Normal ALT (AASLD) | 79% | 75%
Normalized ALT (Central Lab) [The population used for analysis of ALT normalization included only subjects with ALT above upper limit of normal (ULN) of the central laboratory range (>43 U/L for males 18 to <69 years and >35 U/L for males ≥69 years; >34 U/L for females 18 to <69 years and >32 U/L for females ≥69 years) at baseline.] , [Proportion of subjects at Week 48: VEMLIDY, 16/32; TDF, 7/19.] | 50% | 37%
Normalized ALT (AASLD) [The population used for analysis of ALT normalization included only subjects with ALT above ULN of the 2018 American Association of the Study of Liver Diseases (AASLD) criteria (35 U/L males and 25 U/L females) at baseline.] , [Proportion of subjects at Week 48: VEMLIDY, 26/52; TDF, 14/53.] | 50% | 26%
Serology
HBeAg Loss / Seroconversion [The population used for serology analysis included only subjects with antigen (HBeAg) positive and anti-body (HBeAb) negative or missing at baseline.] | 8% / 3% | 6% / 0
HBsAg Loss / Seroconversion | 0 / 0 | 2% / 0

14.4 Clinical Trial in Adults with Chronic Hepatitis B Virus Infection and Renal Impairment

In Trial 4035, Part A, the efficacy and safety of switching from TDF and/or other antivirals to VEMLIDY were evaluated in an open-label clinical trial of virologically suppressed chronic hepatitis B infected adults with moderate to severe renal impairment (estimated creatinine clearance between 15 and 59 mL per minute by Cockcroft-Gault method) (Cohort 1, N=78) or ESRD (estimated creatinine clearance below 15 mL per minute by Cockcroft-Gault method) on hemodialysis (Cohort 2, N=15). At baseline, 98% of subjects in Part A had baseline HBV DNA <20 IU/mL. Median age was 65 years, 74% were male, 77% were Asian, 16% were White, and 83% were HBeAg-negative. Previous treatment with oral antivirals included TDF (Cohort 1, N=57; Cohort 2, N=1), lamivudine (N=46), adefovir dipivoxil (N=46), and entecavir (N=43). At baseline, 97% and 95% of subjects had ALT ≤ULN based on central laboratory criteria and 2018 AASLD criteria, respectively; median estimated creatinine clearance by Cockcroft-Gault was 43 mL per minute (45 mL per minute in Cohort 1 and 7 mL per minute in Cohort 2); and 34% of subjects had a history of cirrhosis.

Overall, 98% of subjects achieved HBV DNA <20 IU/mL at Week 24 (Cohort 1, 97%; Cohort 2, 100%). Two subjects in Cohort 1 discontinued treatment early (due to subject decision); last available HBV DNA for both of these subjects was <20 IU/mL. The overall mean (SD) change from baseline in ALT values was +1 (11.3) U/L (Cohort 1, +1 [11.9] U/L; Cohort 2, +3 [7.9] U/L) at Week 24. No subject had HBeAg or HBsAg loss at Week 24. The mean (SD) changes in HBsAg level from baseline were -0.05 (0.122) log10 IU/mL (-0.05 [0.124] log10 IU/mL for Cohort 1 and -0.07 [0.115] log10 IU/mL for Cohort 2) at Week 24.

14.5 Clinical Trial in Pediatric Subjects 6 Years of Age and Older with Chronic Hepatitis B Virus Infection

In Trial 1092, the efficacy and safety of VEMLIDY in chronic HBV-infected subjects were evaluated in a randomized, double-blind, placebo-controlled clinical trial of treatment-naïve and treatment-experienced subjects between the ages of 12 to less than 18 years weighing at least 35 kg (Cohort 1; N=70) and 6 to less than 12 years weighing at least 25 kg (Cohort 2, Group 1; N=18). Subjects were randomized to receive VEMLIDY (N=59) or placebo (N=29) once daily. Baseline demographics and HBV disease characteristics were comparable between the VEMLIDY treatment arm and the placebo arm: in the VEMLIDY group, 58% were male, 63% were Asian, and 27% were White; 9%, 24%, 22%, and 44% had HBV genotype A, B, C, and D, respectively; 98% percent were HBeAg positive. At baseline, overall median HBV DNA was 8.1 log10 IU/mL, mean ALT was 107 U/L, median HBsAg was 4.5 log10 IU/mL. Previous treatment included oral antivirals (N=20 [23%]), including entecavir (N=10 [11%]), lamivudine (N=10 [11%]), and TDF (N=2 [2%]), and/or interferons (N=13 [15%]).

The results for each treatment group and cohort for HBV DNA < 20 IU/mL at Weeks 24, 48 and 96 are presented in Table 16 below.

Table 16 Trial 1092: HBV DNA Virologic Outcome in Pediatric Subjects 6 Years of Age and Older with Chronic HBV
 | TAF (N=59) | PBO-TAF (N=29)
HBV DNA <20 IU/mL at Week 24 (total) | 11/59 (19%) | 0/29
- Cohort 1 (12– <18 and at least 35 kg) | 10/47 (21%) | 0/23
- Cohort 2 Group 1 (6– <12 and at least 25 kg) | 1/12 (8%) | 0/6
HBV DNA <20 IU/mL at Week 48 (total) | 22/59 (37%) | 6/29 (21%) [Week 24 on TAF]
- Cohort 1 (12– <18 and at least 35 kg) | 19/47 (40%) | 5/23 (22)
- Cohort 2 Group 1 (6– <12 and at least 25 kg) | 3/12 (25%) | 1/6 (17%)
HBV DNA <20 IU/mL at Week 96 (total) | 36/59 (61%) | 14/29 (48%) [Week 72 on TAF]
- Cohort 1 (12– <18 and at least 35 kg) | 30/47 (64%) | 12/23 (52%)
- Cohort 2 Group 1 (6– <12 and at least 25 kg) | 6/12 (50%) | 2/6 (33%)

At Week 96, the overall mean (SD) change from baseline in HBV DNA for VEMLIDY-treated subjects and subjects who switched from placebo to VEMLIDY, respectively, was -6.18 (1.495) log10 IU/mL and -5.92 (1.775) log10 IU/mL. The overall median change from baseline in ALT values for the VEMLIDY and placebo-VEMLIDY treatment groups, respectively, was -39.5 U/L and -46.5 U/L at Week 96. ALT normalization (AASLD criteria) was achieved for 54% of VEMLIDY-treated subjects and 57% of subjects who switched from placebo to VEMLIDY.

At Week 96, 14/58 (24%) VEMLIDY-treated subjects and 5/29 (17%) subjects who switched from placebo to VEMLIDY experienced HBeAg loss with anti-HBe seroconversion. One of 47 (2%) subjects in the Cohort 1 VEMLIDY group achieved HBsAg loss at Week 96.

16 HOW SUPPLIED/STORAGE AND HANDLING

VEMLIDY tablets containing 25 mg of tenofovir alafenamide are yellow, round, film-coated, debossed with "GSI" on one side and "25" on the other side. Each bottle contains 30 tablets (NDC 61958-2301-1), a silica gel desiccant, polyester coil, and is closed with a child-resistant closure.

STORAGE AND HANDLING

Store below 30 °C (86 °F).

- Keep container tightly closed.
- Dispense only in original container.

17 PATIENT COUNSELING INFORMATION

Advise the patient to read the FDA-approved patient labeling (Patient Information).

Severe Acute Exacerbation of Hepatitis after Discontinuation of Treatment

Inform patients that discontinuation of anti-hepatitis B therapy, including VEMLIDY, may result in severe acute exacerbations of hepatitis B. Advise the patient to not discontinue VEMLIDY without first informing their healthcare provider [see Warnings and Precautions (5.1)].

Risk of Development of HIV-1 Resistance in Patients with HIV-1 Coinfection

Inform patients that if they have or develop HIV infection and are not receiving effective HIV treatment, VEMLIDY may increase the risk of development of resistance to HIV medication [see Dosage and Administration (2.1) and Warnings and Precautions (5.2)].

New Onset or Worsening Renal Impairment

Postmarketing cases of renal impairment, including acute renal failure, have been reported [see Warnings and Precautions (5.3)].

Lactic Acidosis and Severe Hepatomegaly

Lactic acidosis and severe hepatomegaly with steatosis, including fatal cases, have been reported with use of drugs similar to VEMLIDY. Advise patients to contact their healthcare provider immediately and stop VEMLIDY if they develop clinical symptoms suggestive of lactic acidosis or pronounced hepatotoxicity [see Warnings and Precautions (5.4)].

Drug Interactions

Advise patients to report to their healthcare provider the use of any other prescription or non-prescription medication or herbal products including St. John's wort, as VEMLIDY may interact with other drugs [see Drug Interactions (7)].

Missed Dosage

Inform patients that it is important to take VEMLIDY on a regular dosing schedule with food and to avoid missing doses, as it can result in development of resistance [see Dosage and Administration (2.2)].

Pregnancy Registry

Inform patients that there is an antiretroviral pregnancy registry to monitor fetal outcomes of pregnant women exposed to VEMLIDY [see Use in Specific Populations (8.1)].

Manufactured and distributed by: Gilead Sciences, Inc. Foster City, CA 94404

© 2024 Gilead Sciences, Inc. All rights reserved.

Patient Information
VEMLIDY® (VEM-lih-dee)
(tenofovir alafenamide)
tablets

What is the most important information I should know about VEMLIDY?
VEMLIDY can cause serious side effects, including:

- Worsening of hepatitis B virus (HBV) infection. Your HBV infection may get worse (flare-up) if you take VEMLIDY and then stop taking it. A "flare-up" is when your HBV infection suddenly returns in a worse way than before.
  - Do not run out of VEMLIDY. Refill your prescription or talk to your healthcare provider before your VEMLIDY is all gone.
  - Do not stop taking VEMLIDY without first talking to your healthcare provider.
  - If you stop taking VEMLIDY, your healthcare provider will need to check your health often and do blood tests regularly for several months to check your liver. Tell your healthcare provider about any new or unusual symptoms you may have after you stop taking VEMLIDY.

For more information about side effects, see the section "What are the possible side effects of VEMLIDY?"

What is VEMLIDY?
VEMLIDY is a prescription medicine used to treat chronic (long-lasting) hepatitis B virus (HBV) in adults and children 6 years of age and older who weigh at least 55 pounds (25 kg) with stable (compensated) liver disease.

- VEMLIDY may lower the amount of HBV in your body.
- VEMLIDY may improve the condition of your liver.

It is not known if VEMLIDY is safe and effective in children with chronic HBV infection who are under 6 years of age or weigh less than 55 pounds (25 kg).

What should I tell my healthcare provider before taking VEMLIDY?
Before taking VEMLIDY, tell your healthcare provider about all of your medical conditions, including if you:

- have HIV-1 infection. Your healthcare provider may test you for HIV-1 infection before you start VEMLIDY. If you have both HBV and HIV-1, and you only take VEMLIDY, the HIV-1 virus may develop resistance and become harder to treat.
- have end stage renal disease (ESRD).
- are pregnant or plan to become pregnant. It is not known if VEMLIDY will harm your unborn baby. Tell your healthcare provider if you become pregnant during treatment with VEMLIDY.
  Pregnancy Exposure Registry: There is a pregnancy registry for women who take antiviral medicines during pregnancy. The purpose of this registry is to collect information about the health of you and your baby. Talk with your healthcare provider about how you can take part in this registry.
- are breastfeeding or plan to breastfeed. VEMLIDY may pass into your breastmilk. Talk with your healthcare provider about the best way to feed your baby.

Tell your healthcare provider about all the medicines you take, including prescription and over-the-counter medicines, vitamins, and herbal supplements.
Some medicines may affect how VEMLIDY works.

- Keep a list of your medicines and show it to your healthcare provider and pharmacist when you get a new medicine. You can ask your healthcare provider or pharmacist for a list of medicines that interact with VEMLIDY.
- Do not start a new medicine without telling your healthcare provider. Your healthcare provider can tell you if it is safe to take VEMLIDY with other medicines.

How should I take VEMLIDY?

- Take VEMLIDY exactly as your healthcare provider tells you to take it.
- Take VEMLIDY 1 time each day.
- Take VEMLIDY with food.
- If you are on dialysis, on your dialysis days, take your daily dose of VEMLIDY following dialysis.
- Do not change your dose or stop taking VEMLIDY without first talking with your healthcare provider. Stay under a healthcare provider's care when taking VEMLIDY.
- Do not miss a dose of VEMLIDY.
- If you take too much VEMLIDY, call your healthcare provider or go to the nearest hospital emergency room right away.
- When your VEMLIDY supply starts to run low, get more from your healthcare provider or pharmacy. This is very important because your HBV infection may get worse (flare-up) if you stop taking VEMLIDY.

What are the possible side effects of VEMLIDY?
VEMLIDY may cause serious side effects, including:

- See "What is the most important information I should know about VEMLIDY?"
- New or worse kidney problems, including kidney failure. Your healthcare provider should do blood and urine tests to check your kidneys when starting and during treatment with VEMLIDY. Your healthcare provider may tell you to stop taking VEMLIDY if you develop new or worse kidney problems.
- Too much lactic acid in your blood (lactic acidosis). Too much lactic acid is a serious but rare medical emergency that can lead to death. Tell your healthcare provider right away if you get these symptoms: weakness or being more tired than usual, unusual muscle pain, being short of breath or fast breathing, stomach pain with nausea and vomiting, cold or blue hands and feet, feel dizzy or lightheaded, or a fast or abnormal heartbeat.
- Severe liver problems. In rare cases, severe liver problems can happen that can lead to death. Tell your healthcare provider right away if you get these symptoms: skin or the white part of your eyes turns yellow, dark "tea-colored" urine, light-colored stools, loss of appetite for several days or longer, nausea, or stomach-area pain.

The most common side effect of VEMLIDY is headache. Tell your healthcare provider if you have any side effect that bothers you or that does not go away.
These are not all the possible side effects of VEMLIDY. For more information, ask your healthcare provider or pharmacist.
Call your doctor for medical advice about side effects. You may report side effects to FDA at 1-800-FDA-1088.

How should I store VEMLIDY?

- Store VEMLIDY below 86 °F (30 °C).
- Keep VEMLIDY in its original container.
- Keep the container tightly closed.
- VEMLIDY comes in a child-resistant package.

Keep VEMLIDY and all medicines out of reach of children.

General information about the safe and effective use of VEMLIDY.
Medicines are sometimes prescribed for purposes other than those listed in a Patient Information leaflet. Do not use VEMLIDY for a condition for which it was not prescribed. Do not give VEMLIDY to other people, even if they have the same symptoms you have. It may harm them. If you would like more information, talk with your healthcare provider. You can ask your healthcare provider or pharmacist for information about VEMLIDY that is written for health professionals.

What are the ingredients in VEMLIDY?
Active ingredients: tenofovir alafenamide
Inactive ingredients: croscarmellose sodium, lactose monohydrate, magnesium stearate, and microcrystalline cellulose. The tablets are film-coated with a coating material containing: iron oxide yellow, polyethylene glycol, polyvinyl alcohol, talc, and titanium dioxide.
Manufactured and distributed by: Gilead Sciences, Inc. Foster City, CA 94404
VEMLIDY is a registered trademark of Gilead Sciences, Inc., or its related companies. © 2024 Gilead Sciences, Inc. All rights reserved.
208464-GS-009
For more information, call 1-800-445-3235 or go to www.VEMLIDY.com.

This Patient Information has been approved by the U.S. Food and Drug Administration.

Revised: 03/2024

PRINCIPAL DISPLAY PANEL - 25 mg Tablet Bottle Label

NDC 61958- 2301-1
30 tablets

Vemlidy®
(tenofovir alafenamide)
tablets, 25 mg

Note to pharmacist:
Do not cover ALERT box with pharmacy label.

ALERT: Find out about medicines that
should NOT be taken with Vemlidy